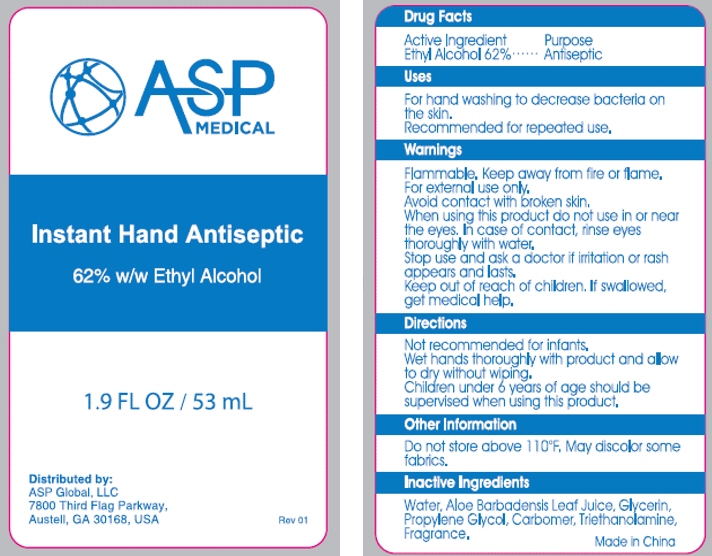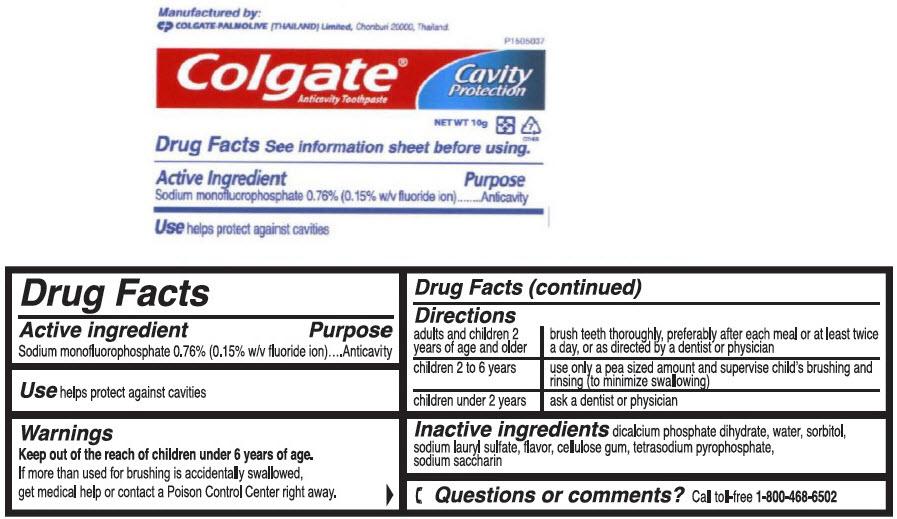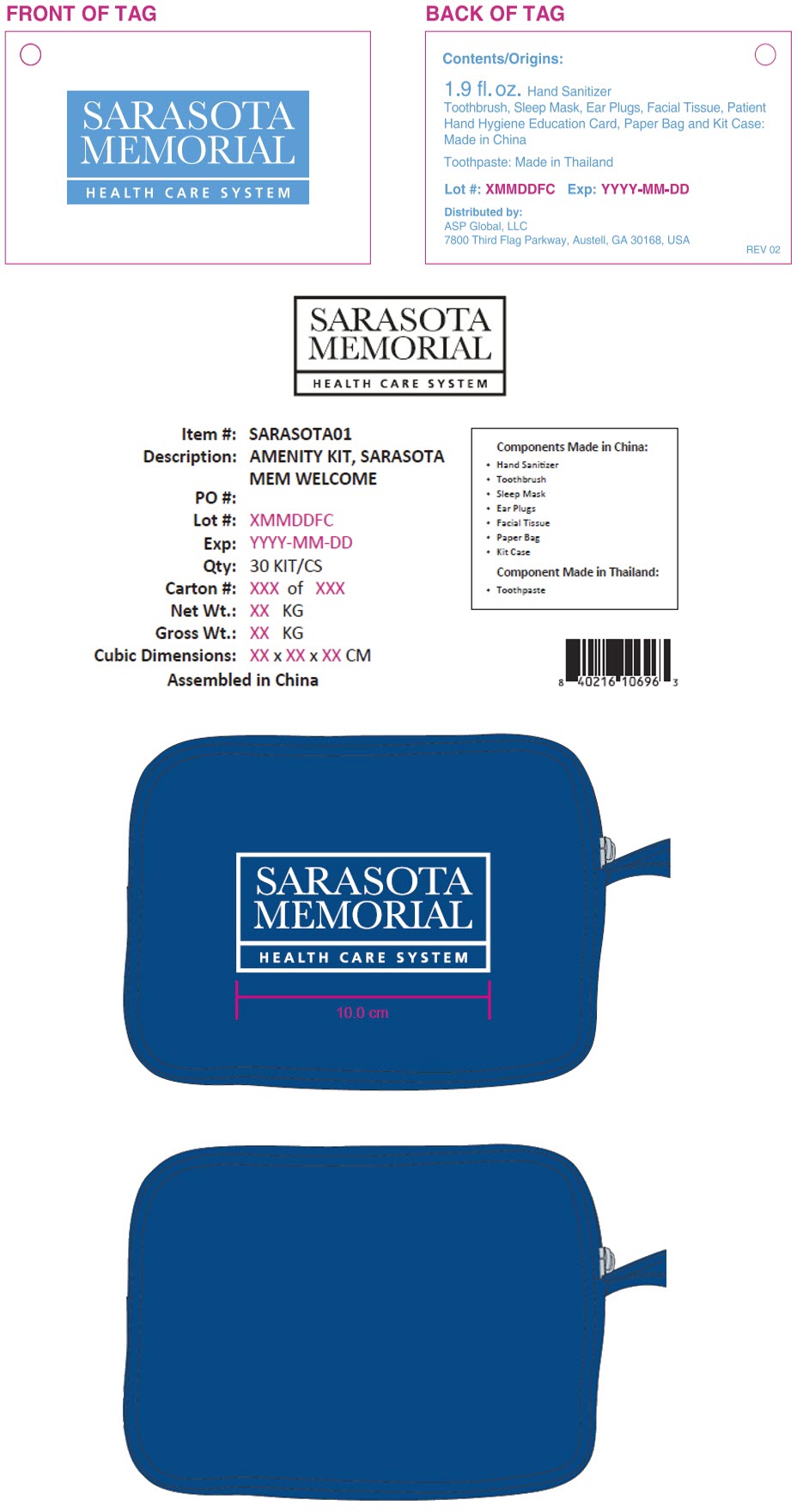 DRUG LABEL: Sarasota Memorial Amenity
NDC: 59448-600 | Form: KIT | Route: TOPICAL
Manufacturer: ASP Global, LLc
Category: otc | Type: HUMAN OTC DRUG LABEL
Date: 20241217

ACTIVE INGREDIENTS: ALCOHOL 62 mL/100 mL; SODIUM MONOFLUOROPHOSPHATE 7.6 mg/1 g
INACTIVE INGREDIENTS: Water; Aloe Vera Leaf; Glycerin; Propylene Glycol; CARBOMER INTERPOLYMER TYPE A (ALLYL SUCROSE CROSSLINKED); Trolamine; DIBASIC CALCIUM PHOSPHATE DIHYDRATE; Water; Sorbitol; Sodium Lauryl Sulfate; SODIUM PYROPHOSPHATE; SACCHARIN SODIUM

Sarasota Memorial Amenity Kit

Colgate® Anticavity Toothpaste

Drug Facts

Active ingredient

Sodium monofluorophosphate 0.76% (0.15% w/v fluoride ion)

Purpose

Anticavity

Use

helps protect against cavities

Warnings

KEEP OUT OF REACH OF CHILDREN

Keep out of the reach of children under 6 years of age.

If more than used for brushing is accidentally swallowed, get medical help or contact a Poison Control Center right away.

Directions

adults and children 2 years of age and older | brush teeth thoroughly, preferably after each meal or at least twice a day, or as directed by a dentist or physician
children 2 to 6 years | use only a pea sized amount and supervise child's brushing and rinsing (to minimize swallowing)
children under 2 years | ask a dentist or physician

Inactive ingredients

dicalcium phosphate dihydrate, water, sorbitol, sodium lauryl sulfate, flavor, cellulose gum, tetrasodium pyrophosphate, sodium saccharin

Questions or comments?

Call toll-free 1-800-468-6502

Manufactured by:
COLGATE-PALMOLIVE (THAILAND) Limited, Chonburi 20000, Thailand.

Instant Hand Antiseptic

Drug Facts

Active Ingredient

Ethyl Alcohol 62%

Purpose

Antiseptic

Uses

For hand washing to decrease bacteria on the skin.

Recommended for repeated use.

Warnings

Flammable. Keep away from fire or flame.

For external use only.

Avoid contact with broken skin.

When using this product do not use in or near the eyes. In case of contact, rinse eyes thoroughly with water.

Stop use and ask a doctor if irritation or rash appears and lasts.

Keep out of reach of children. If swallowed, get medical help.

Directions

Not recommended for infants.

Wet hands thoroughly with product and allow to dry without wiping.

Children under 6 years of age should be supervised when using this product.

Other Information

Do not store above 110°F. May discolor some fabrics.

Inactive Ingredients

Water, Aloe Barbadensis Leaf Juice, Glycerin, Propylene Glycol, Carbomer, Triethanolamine, Fragrance.

Distributed by:
ASP Global, LLC
7800 Third Flag Parkway,
Austell, GA 30168, USA

PRINCIPAL DISPLAY PANEL - 53 mL Bottle Label

ASP
MEDICAL

Instant Hand Antiseptic
62% w/w Ethyl Alcohol

1.9 FL OZ / 53 mL

Distributed by:
ASP Global, LLC
7800 Third Flag Parkway,
Austell, GA 30168, USA

Rev 01

PRINCIPAL DISPLAY PANEL - 10 g Tube Label

P1505037

Colgate®
Anticavity Toothpaste

Cavity
Protection

NET WT 10g
7
OTHER

PRINCIPAL DISPLAY PANEL - Kit Label

SARASOTA
MEMORIAL
HEALTH CARE SYSTEM

Contents/Origins:

1.9 fl. oz. Hand Sanitizer
Toothbrush, Sleep Mask, Ear Plugs, Facial Tissue, Patient
Hand Hygiene Education Card, Paper Bag and Kit Case:
Made in China

Toothpaste: Made in Thailand

Lot #: XMMDDFC
Exp: YYYY-MM-DD

Distributed by:
ASP Global, LLC
7800 Third Flag Parkway, Austell, GA 30168, USA

REV 02

SARASOTA
MEMORIAL
HEALTH CARE SYSTEM

Item #: SARASOTA01
Description: AMENITY KIT, SARASOTA
MEM WELCOME
PO #:
Lot #: XMMDDFC
Exp: YYYY-MM-DD
Qty: 30 KIT/CS
Carton #: XXX of XXX
Net Wt.: XX KG
Gross Wt.: XX KG
Cubic Dimensions: XX x XX x XX CM
Assembled in China

Components Made in China:

- Hand Sanitizer
- Toothbrush
- Sleep Mask
- Ear Plugs
- Facial Tissue
- Paper Bag
- Kit Case

Component Made in Thailand:

- Toothpaste

SARASOTA
MEMORIAL
HEALTH CARE SYSTEM